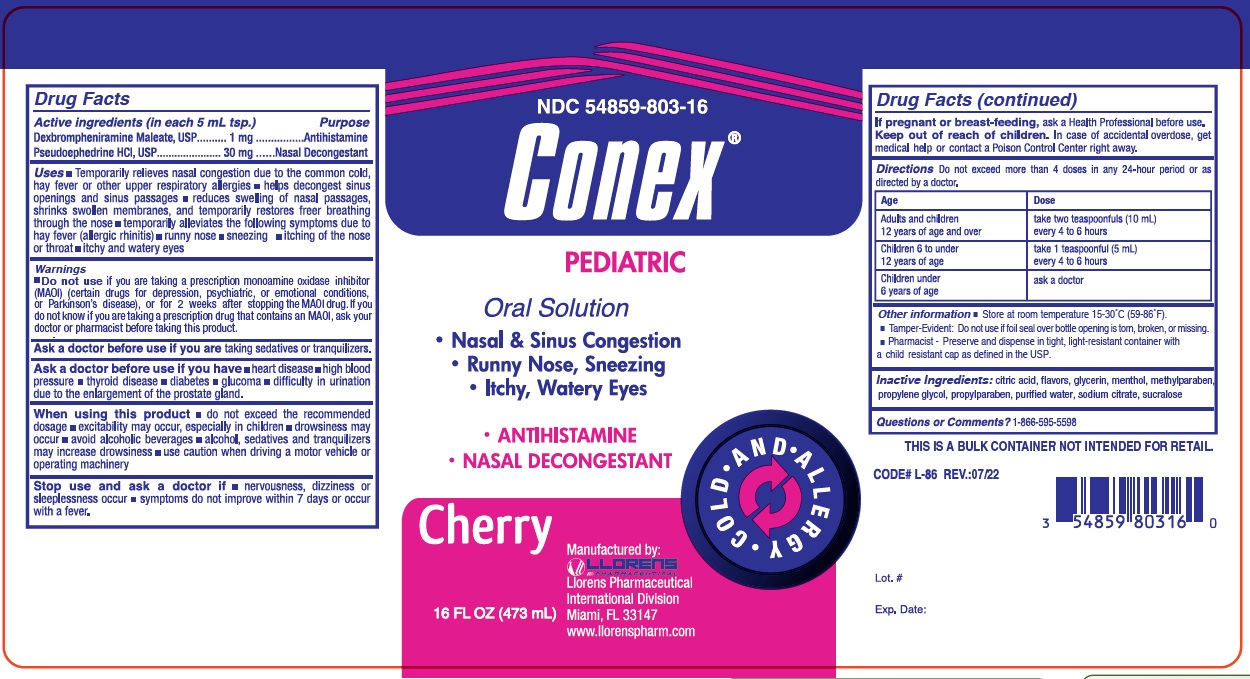 DRUG LABEL: Conex Pediatric
NDC: 54859-803 | Form: LIQUID
Manufacturer: Llorens Pharmaceutical International Division
Category: otc | Type: HUMAN OTC DRUG LABEL
Date: 20251231

ACTIVE INGREDIENTS: DEXBROMPHENIRAMINE MALEATE 1 mg/5 mL; PSEUDOEPHEDRINE HYDROCHLORIDE 30 mg/5 mL
INACTIVE INGREDIENTS: CITRIC ACID MONOHYDRATE; GLYCERIN; MENTHOL; METHYLPARABEN; WATER; PROPYLENE GLYCOL; PROPYLPARABEN; SODIUM CITRATE; SUCRALOSE

Llorens-ConexPed 803

Active Ingredients (in each 5 mL tsp.)

Dexbrompheniramine Maleate, USP .......... 1 mg .................... Antihistamine

Pseudoephedrine HCL, USP ............ 30 mg ...................... Nasal Decongestant

PURPOSE

Antihistamine

Nasal Decongestant

Uses

- Temporarily relieves nasal congestion due to the common cold, hay fever or other upper repiratory allergies
- helps decongest sinus opening and sinus passages
- reduces swelling of nasal passages, shrinks swollen membranes, and temporarily restores freer breathing through the nose
- temporarily alleviates the following symptoms due to hay fever (allergic rhinitis)
- runny nose
- sneezing
- itching of the nose or throat
- ithy and watery eyes

Warnings:

- Do not use ifyou are taking a prescription monoamine oxidase inhibitor (MAOI) (certain drugs for depression, psychiatric, or emotional conditions, or Parkinson's disease), or for 2 weeks after stopping the MAOI drug. If you do not know if you are taking a prescription drug that contains an MAOI, ask your doctor or pharmacist before taking this product.

Ask a doctor before use if you aretaking sedatives or tranquilizers.

Ask a doctor before use if you have

- heart disease
- high blood pressure
- thyroid disese
- diabetes
- difficulty in urination due to the enlargement of the prostate gland.

When using this product

- do not exceed the recommended dosage
- excitability may occur, especially in children
- drowsiness may occur
- avoid alcoholic beverages
- alcohol, sedatives and tranquilizers may increase drowsiness
- use caution when driving a motor vehicle or operating machinery

Stop use and ask a doctor if

- nervousness, dizziness or sleeplessness occur
- symptoms do not improve within 7 days or occur with a fever.

KEEP OUT OF REACH OF CHILDREN

Keep out of the reach of children.In case of overdose, get medical help or contact a Poison Control Center right away.

PREGNANCY OR BREAST FEEDING

If pregnant or breast-feeding,ask a Health Professional before use.

DOSAGE AND ADMINISTRATION

Directions:Do not exceed more than 4 doses in any 24-hour period or as directed by a doctor.

Age | Dose
Adults and children 12 years of age and over | take two teaspoonfuls (10 mL) every 4 to 6 hours
Children under 12 years of age | take 1 teaspoonful (5 mL) every 4 to 6 hours
Children under 6 years of age | ask a doctor

INACTIVE INGREDIENT

Inactive Ingredients: citric acid, flavor, glycerine, menthol, methylparaben, propylene glycol, propylparaben, purified water, sodium citrate and sucralose

Questions or Comments? 1-866-595-5598